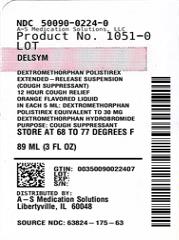 DRUG LABEL: DELSYM
NDC: 50090-0224 | Form: SUSPENSION, EXTENDED RELEASE
Manufacturer: A-S Medication Solutions
Category: otc | Type: HUMAN OTC DRUG LABEL
Date: 20250228

ACTIVE INGREDIENTS: DEXTROMETHORPHAN 30 mg/5 mL
INACTIVE INGREDIENTS: Polistirex; CITRIC ACID; edetate disodium; ETHYLCELLULOSE; KI5; high fructose corn syrup; methylparaben; PEG-75; PEG-20 SORBITAN OLEATE; propylene glycol; propylparaben; AQUA; sucrose; tragacanth; xanthan gum

DELSYM

Drug Facts

Active ingredient (in each 5 mL)

Dextromethorphan polistirex equivalent to 30 mg dextromethorphan hydrobromide

Purpose

Cough suppressant

Uses

temporarily relieves

- cough due to minor throat and bronchial irritation as may occur with the common cold or inhaled irritants
- the impulse to cough to help you get to sleep

Warnings

Do not use if you are now taking a prescription monoamine oxidase inhibitor (MAOI) (certain drugs for depression, psychiatric, or emotional conditions, or Parkinson's disease), or for 2 weeks after stopping the MAOI drug. If you do not know if your prescription drug contains an MAOI, ask a doctor or pharmacist before taking this product.

Ask a doctor before use if you have

- chronic cough that lasts such as occurs with smoking, asthma, or emphysema
- cough that occurs with too much phlegm (mucus)

Stop use and ask a doctor if cough lasts more than 7 days, comes back, or occurs with fever, rash, or headache that lasts. These could be signs of a serious condition.

PREGNANCY OR BREAST FEEDING

If pregnant or breast-feeding, ask a health professional before use.

Keep out of reach of children. In case of overdose, get medical help or contact a Poison Control Center right away.

Directions

- shake bottle well before use
- measure only with dosing cup provided
- do not use dosing cup with other products
- dose as follows or as directed by a doctor

adults and children 12 years of age and over | 10 mL every 12 hours, not to exceed 20 mL in 24 hours
children 6 to under 12 years of age | 5 mL every 12 hours, not to exceed 10 mL in 24 hours
children 4 to under 6 years of age | 2.5 mL every 12 hours, not to exceed 5 mL in 24 hours
children under 4 years of age | do not use

Other information

- each 5 mL contains: sodium 7 mg
- store at 20-25°C (68-77°F)
- dosing cup provided

Inactive ingredients

citric acid, edetate disodium, ethylcellulose, FD&C yellow no. 6, flavor, high fructose corn syrup, methylparaben, partially hydrogenated vegetable oil (soybean, cottonseed), polyethylene glycol 3350, polysorbate 80, propylene glycol, propylparaben, purified water, sucrose, tragacanth, xanthan gum

Questions?

1-866-682-4639
You may also report side effects to this phone number.

Distributed by:
RB Health (US)
Parsippany, NJ
07054-0224

HOW SUPPLIED

Product: 50090-0224

NDC: 50090-0224-0 89 mL in a BOTTLE / 1 in a CARTON